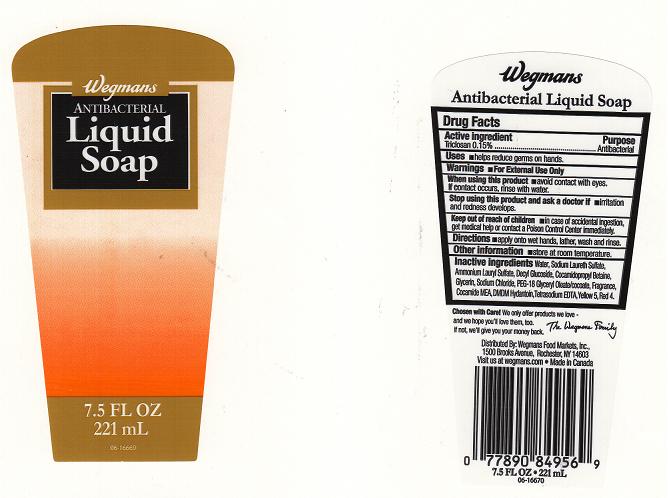 DRUG LABEL: WEGMANS
NDC: 47124-294 | Form: LIQUID
Manufacturer: WEGMANS FOOD MARKETS INC.
Category: otc | Type: HUMAN OTC DRUG LABEL
Date: 20120416

ACTIVE INGREDIENTS: TRICLOSAN 0.15 mL/100 mL
INACTIVE INGREDIENTS: WATER; SODIUM LAURETH SULFATE; AMMONIUM LAURYL SULFATE; DECYL GLUCOSIDE; COCAMIDOPROPYL BETAINE; GLYCERIN; SODIUM CHLORIDE; POLYETHYLENE GLYCOL 900; COCO MONOETHANOLAMIDE; DMDM HYDANTOIN; EDETATE SODIUM; FD&C YELLOW NO. 5; FD&C RED NO. 4

DRUG FACTS

ACTIVE INGREDIENT

TRICLOSAN 0.15%

PURPOSE

ANTIBACTERIAL

USES

HELPS REDUCE GERMS ON HANDS.

WARNINGS

FOR EXTERNAL USE ONLY.

WHEN USING THIS PRODUCT

AVOID CONTACT WITH EYES. IF CONTACT OCCURS, RINSE WITH WATER.

STOP USING THIS PRODUCT AND ASK A DOCTOR IF

IRRITATION AND REDNESS DEVELOPS.

KEEP OUT OF REACH OF CHILDREN

IN CASE OF ACCIDENTAL INGESTION, GET MEDICAL HELP OR CONTACT A POISON CONTROL CENTER IMMEDIATELY.

DIRECTIONS

APPLY ONTO WET HANDS, LATHER, WASH AND RINSE.

OTHER INFORMATION

STORE AT ROOM TEMPERATURE.

INACTIVE INGREDIENTS

WATER, SODIUM LAURETH SULFATE, AMMONIUM LAURYL SULFATE, DECYL GLUCOSIDE, COCAMIDOPROPYL BETAINE, GLYCERIN, SODIUM CHLORIDE, PEG-18 GLYCERYL OLEATE/COCOATE, FRAGRANCE, COCAMIDE MEA, DMDM HYDANTOIN, TETRASODIUM EDTA, YELLOW 5, RED 4.